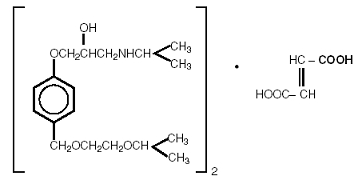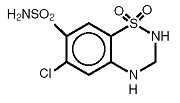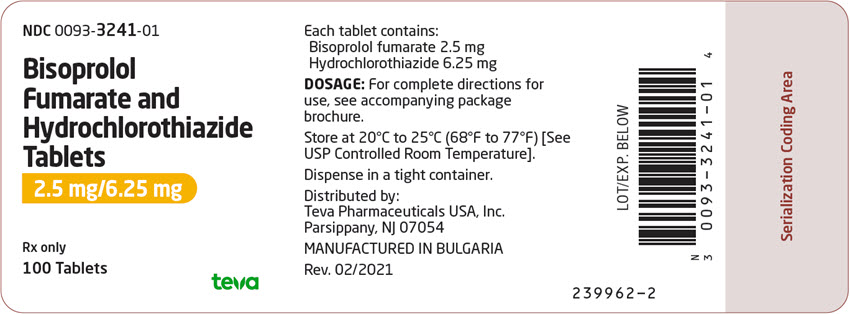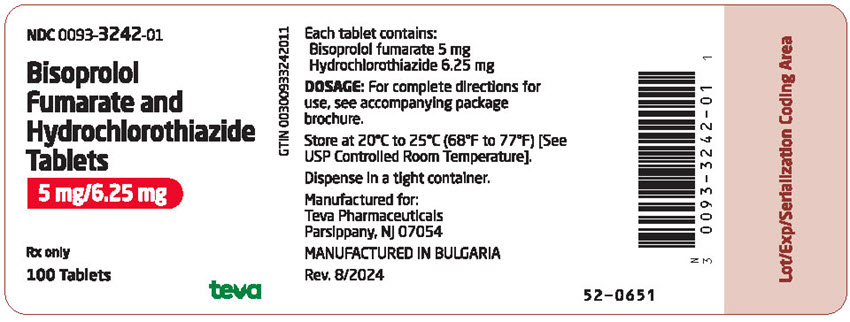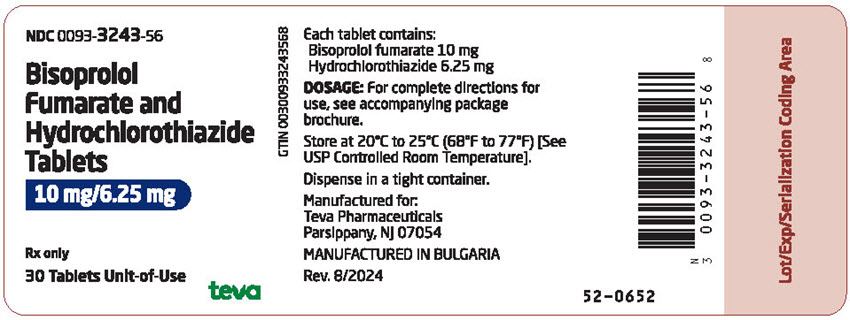 DRUG LABEL: bisoprolol fumarate and hydrochlorothiazide
NDC: 0093-3241 | Form: TABLET, FILM COATED
Manufacturer: Teva Pharmaceuticals USA, Inc.
Category: prescription | Type: HUMAN PRESCRIPTION DRUG LABEL
Date: 20250814

ACTIVE INGREDIENTS: BISOPROLOL FUMARATE 2.5 mg/1 1; HYDROCHLOROTHIAZIDE 6.25 mg/1 1
INACTIVE INGREDIENTS: STARCH, CORN; ANHYDROUS DIBASIC CALCIUM PHOSPHATE; HYPROMELLOSES; MAGNESIUM STEARATE; CELLULOSE, MICROCRYSTALLINE; POLYETHYLENE GLYCOL, UNSPECIFIED; POLYSORBATE 80; TITANIUM DIOXIDE; CROSPOVIDONE (15 MPA.S AT 5%); FERRIC OXIDE YELLOW

Bisoprolol Fumarate and Hydrochlorothiazide Tablets

Rx only

DESCRIPTION

Bisoprolol fumarate and hydrochlorothiazide tablets are indicated for the treatment of hypertension. It combines two antihypertensive agents in a once-daily dosage: a synthetic beta1-selective (cardioselective) adrenoceptor blocking agent (bisoprolol fumarate) and a benzothiadiazine diuretic (hydrochlorothiazide).

Bisoprolol fumarate is chemically described as (±)-1-[4-[[2-(1-methylethoxy)ethoxy]methyl]phenoxy]-3-[(1-methylethyl)amino]-2-propanol(E)-2-butenedioate (2:1) (salt). It possesses an asymmetric carbon atom in its structure and is provided as a racemic mixture. The S(-) enantiomer is responsible for most of the beta-blocking activity. Its empirical formula is (C18H31NO4)2•C4H4O4 and it has a molecular weight of 766.97. Its structural formula is:

Bisoprolol fumarate is a white crystalline powder, approximately equally hydrophilic and lipophilic, and readily soluble in water, methanol, ethanol, and chloroform.

Hydrochlorothiazide (HCTZ) is 6-Chloro-3,4-dihydro-2H-1,2,4-benzothiadiazine-7-sulfonamide 1,1-dioxide. It is a white, or practically white, practically odorless crystalline powder. It is slightly soluble in water, sparingly soluble in dilute sodium hydroxide solution, freely soluble in n-butylamine and dimethylformamide, sparingly soluble in methanol, and insoluble in ether, chloroform, and dilute mineral acids. Its empirical formula is C7H8ClN3O4S2 and it has a molecular weight of 297.73. Its structural formula is:

Each bisoprolol fumarate and hydrochlorothiazide tablet - 2.5 mg/6.25 mg tablet for oral administration contains:

Bisoprolol fumarate…………………………………………..2.5 mg

Hydrochlorothiazide………………………………………..6.25 mg

Each bisoprolol fumarate and hydrochlorothiazide tablet - 5 mg/6.25 mg tablet for oral administration contains:

Bisoprolol fumarate……………………………………………5 mg

Hydrochlorothiazide………………………………………..6.25 mg

Each bisoprolol fumarate and hydrochlorothiazide tablet - 10 mg/6.25 mg tablet for oral administration contains:

Bisoprolol fumarate…………………………………………...10 mg

Hydrochlorothiazide………………………………………..6.25 mg

Inactive ingredients include Corn Starch, Dibasic Calcium Phosphate, Hypromellose, Magnesium Stearate, Microcrystalline Cellulose, Polyethylene Glycol, Polysorbate 80, and Titanium Dioxide. The 10 mg/6.25mg tablet also contains Colloidal Silicon Dioxide. The 5 mg/6.25 mg tablet also contains Colloidal Silicon Dioxide, and Red and Yellow Iron Oxide. The 2.5 mg/6.25 mg tablet also contains Crospovidone, Pregelatinized Starch, and Yellow Iron Oxide.

CLINICAL PHARMACOLOGY

Bisoprolol fumarate and HCTZ have been used individually and in combination for the treatment of hypertension. The antihypertensive effects of these agents are additive; HCTZ 6.25 mg significantly increases the antihypertensive effect of bisoprolol fumarate. The incidence of hypokalemia with the bisoprolol fumarate and HCTZ 6.25 mg combination (B/H) is significantly lower than with HCTZ 25 mg. In clinical trials of bisoprolol fumarate and hydrochlorothiazide tablets, mean changes in serum potassium for patients treated with bisoprolol fumarate and hydrochlorothiazide tablets 2.5/6.25 mg, 5/6.25 mg or 10/6.25 mg or placebo were less than ± 0.1 mEq/L. Mean changes in serum potassium for patients treated with any dose of bisoprolol in combination with HCTZ 25 mg ranged from -0.1 to -0.3 mEq/L.

Bisoprolol fumarate is a beta1-selective (cardioselective) adrenoceptor blocking agent without significant membrane stabilizing or intrinsic sympathomimetic activities in its therapeutic dose range. At higher doses (≥20 mg) bisoprolol fumarate also inhibits beta2-adrenoreceptors located in bronchial and vascular musculature. To retain relative selectivity, it is important to use the lowest effective dose.

Hydrochlorothiazide is a benzothiadiazine diuretic. Thiazides affect renal tubular mechanisms of electrolyte reabsorption and increase excretion of sodium and chloride in approximately equivalent amounts. Natriuresis causes a secondary loss of potassium.

Pharmacokinetics and Metabolism

Bisoprolol Fumarate and Hydrochlorothiazide Tablets

In healthy volunteers, both bisoprolol fumarate and hydrochlorothiazide are well absorbed following oral administration of bisoprolol fumarate and hydrochlorothiazide tablets. No change is observed in the bioavailability of either agent when given together in a single tablet. Absorption is not affected whether bisoprolol fumarate and hydrochlorothiazide tablets are taken with or without food. Mean peak bisoprolol fumarate plasma concentrations of about 9.0 ng/mL, 19 ng/mL and 36 ng/mL occur approximately 3 hours after the administration of the 2.5 mg/6.25 mg, 5 mg/6.25 mg and 10 mg/6.25 mg combination tablets, respectively. Mean peak plasma hydrochlorothiazide concentrations of 30 ng/mL occur approximately 2.5 hours following the administration of the combination. Dose proportional increases in plasma bisoprolol concentrations are observed between the 2.5 and 5, as well as between the 5 and 10 mg doses. The elimination T1/2 of bisoprolol ranges from 7 to 15 hours, and that of hydrochlorothiazide ranges from 4 to 10 hours. The percent of dose excreted unchanged in urine is about 55% for bisoprolol and about 60% for hydrochlorothiazide.

Bisoprolol Fumarate

The absolute bioavailability after a 10 mg oral dose of bisoprolol fumarate is about 80%. The first pass metabolism of bisoprolol fumarate is about 20%.

The pharmacokinetic profile of bisoprolol fumarate has been examined following single doses and at steady state. Binding to serum proteins is approximately 30%. Peak plasma concentrations occur within 2-4 hours of dosing with 2.5 to 20 mg, and mean peak values range from 9.0 ng/mL at 2.5 mg to 70 ng/mL at 20 mg. Once-daily dosing with bisoprolol fumarate results in less than twofold intersubject variation in peak plasma concentrations. Plasma concentrations are proportional to the administered dose in the range of 2.5 to 20 mg. The plasma elimination half-life is 9-12 hours and is slightly longer in elderly patients, in part because of decreased renal function. Steady state is attained within 5 days with once-daily dosing. In both young and elderly populations, plasma accumulation is low; the accumulation factor ranges from 1.1 to 1.3 and is what would be expected from the half-life and once-daily dosing. Bisoprolol is eliminated equally by renal and nonrenal pathways with about 50% of the dose appearing unchanged in the urine and the remainder in the form of inactive metabolites. In humans, the known metabolites are labile or have no known pharmacologic activity. Less than 2% of the dose is excreted in the feces. The pharmacokinetic characteristics of the two enantiomers are similar. Bisoprolol is not metabolized by cytochrome P450 II D6 (debrisoquin hydroxylase).

In subjects with creatinine clearance less than 40 mL/min, the plasma half-life is increased approximately threefold compared to healthy subjects.

In patients with liver cirrhosis, the rate of elimination of bisoprolol is more variable and significantly slower than that in healthy subjects, with a plasma half-life ranging from 8 to 22 hours.

In elderly subjects, mean plasma concentrations at steady state are increased, in part attributed to lower creatinine clearance. However, no significant differences in the degree of bisoprolol accumulation is found between young and elderly populations.

Hydrochlorothiazide

Hydrochlorothiazide is well absorbed (65%-75%) following oral administration. Absorption of hydrochlorothiazide is reduced in patients with congestive heart failure.

Peak plasma concentrations are observed within 1-5 hours of dosing and range from 70-490 ng/mL following oral doses of 12.5-100 mg. Plasma concentrations are linearly related to the administered dose. Concentrations of hydrochlorothiazide are 1.6-1.8 times higher in whole blood than in plasma. Binding to serum proteins has been reported to be approximately 40% to 68%. The plasma elimination half-life has been reported to be 6-15 hours. Hydrochlorothiazide is eliminated primarily by renal pathways. Following oral doses of 12.5-100 mg, 55%-77% of the administered dose appears in urine and greater than 95% of the absorbed dose is excreted in urine as unchanged drug. Plasma concentrations of hydrochlorothiazide are increased, and the elimination half-life is prolonged in patients with renal disease.

Pharmacodynamics

Bisoprolol Fumarate

Findings in clinical hemodynamics studies with bisoprolol fumarate are similar to those observed with other beta-blockers. The most prominent effect is the negative chronotropic effect, giving a reduction in resting and exercise heart rate. There is a fall in resting and exercise cardiac output with little observed change in stroke volume, and only a small increase in right atrial pressure, or pulmonary capillary wedge pressure at rest or during exercise.

In normal volunteers, bisoprolol fumarate therapy resulted in a reduction of exercise- and isoproterenol-induced tachycardia. The maximal effect occurred within 1-4 hours post-dosing. Effects generally persisted for 24 hours at doses of 5 mg or greater.

In controlled clinical trials, bisoprolol fumarate given as a single daily dose has been shown to be an effective antihypertensive agent when used alone or concomitantly with thiazide diuretics (see CLINICAL STUDIES).

The mechanism of bisoprolol fumarate’s antihypertensive effect has not been completely established. Factors that may be involved include:

1. Decreased cardiac output,
2. Inhibition of renin release by the kidneys,
3. Diminution of tonic sympathetic outflow from vasomotor centers in the brain.

Beta1-selectivity of bisoprolol fumarate has been demonstrated in both animal and human studies. No effects at therapeutic doses on beta2-adrenoreceptor density have been observed. Pulmonary function studies have been conducted in healthy volunteers, asthmatics, and patients with chronic obstructive pulmonary disease (COPD). Doses of bisoprolol fumarate ranged from 5 to 60 mg, atenolol from 50 to 200 mg, metoprolol from 100 to 200 mg, and propranolol from 40 to 80 mg. In some studies, slight, asymptomatic increases in airway resistance (AWR) and decreases in forced expiratory volume (FEV1) were observed with doses of bisoprolol fumarate 20 mg and higher, similar to the small increases in AWR noted with other cardioselective beta-blocking agents. The changes induced by beta-blockade with all agents were reversed by bronchodilator therapy.

Electrophysiology studies in man have demonstrated that bisoprolol fumarate significantly decreases heart rate, increases sinus node recovery time, prolongs AV node refractory periods, and, with rapid atrial stimulation, prolongs AV nodal conduction.

Hydrochlorothiazide

Acute effects of thiazides are thought to result from a reduction in blood volume and cardiac output, secondary to a natriuretic effect, although a direct vasodilatory mechanism has also been proposed. With chronic administration, plasma volume returns toward normal, but peripheral vascular resistance is decreased.

Thiazides do not affect normal blood pressure. Onset of action occurs within 2 hours of dosing, peak effect is observed at about 4 hours, and activity persists for up to 24 hours.

CLINICAL STUDIES

In controlled clinical trials, bisoprolol fumarate/hydrochlorothiazide 6.25 mg has been shown to reduce systolic and diastolic blood pressure throughout a 24-hour period when administered once daily. The effects on systolic and diastolic blood pressure reduction of the combination of bisoprolol fumarate and hydrochlorothiazide were additive. Further, treatment effects were consistent across age groups (<60, ≥ 60 years), racial groups (black, nonblack), and gender (male, female).

In two randomized, double-blind, placebo-controlled trials conducted in the U.S., reductions in systolic and diastolic blood pressure and heart rate 24 hours after dosing in patients with mild-to-moderate hypertension are shown below. In both studies mean systolic/diastolic blood pressure and heart rate at baseline were approximately 151/101 mm Hg and 77 bpm.

Sitting Systolic/Diastolic Pressure (BP) and Heart Rate (HR)
 | Mean Decrease (Δ) After 3-4 Weeks
 | Study 1 |  | Study 2
 | Placebo | B5/H6.25 mg | Placebo | H6.25 mg | B2.5/H6.25 mg | B10/H6.25 mg
n= | 75 | 150 | 56 | 23 | 28 | 25
Total ΔBP (mm Hg) | -2.9/-3.9 | -15.8/-12.6 | -3.0/-3.7 | -6.6/-5.8 | -14.1/-10.5 | -15.3/-14.3
Drug Effecta | -/- | -12.9/-8.7 | -/- | -3.6/-2.1 | -11.1/-6.8 | -12.3/-10.6
Total ΔHR (bpm) | -0.3 | -6.9 | -1.6 | -0.8 | -3.7 | -9.8
Drug Effecta | - | -6.6 | - | +0.8 | -2.1 | -8.2

a Observed mean change from baseline minus placebo.

Blood pressure responses were seen within 1 week of treatment but the maximum effect was apparent after 2 to 3 weeks of treatment. Overall, significantly greater blood pressure reductions were observed on bisoprolol fumarate and hydrochlorothiazide tablets than on placebo. Further, blood pressure reductions were significantly greater for each of the bisoprolol fumarate plus hydrochlorothiazide combinations than for either of the components used alone regardless of race, age, or gender. There were no significant differences in response between black and nonblack patients.

INDICATIONS AND USAGE

Bisoprolol fumarate and hydrochlorothiazide tablets are indicated in the management of hypertension.

CONTRAINDICATIONS

Bisoprolol fumarate and hydrochlorothiazide tablets are contraindicated in patients in cardiogenic shock, overt cardiac failure (see WARNINGS), second or third degree AV block, marked sinus bradycardia, anuria, and hypersensitivity to either component of this product or to other sulfonamide-derived drugs.

WARNINGS

Cardiac Failure

In general, beta-blocking agents should be avoided in patients with overt congestive failure. However, in some patients with compensated cardiac failure, it may be necessary to utilize these agents. In such situations, they must be used cautiously.

Patients Without a History of Cardiac Failure

Continued depression of the myocardium with beta-blockers can, in some patients, precipitate cardiac failure. At the first signs or symptoms of heart failure, discontinuation of bisoprolol fumarate and hydrochlorothiazide tablets should be considered. In some cases bisoprolol fumarate and hydrochlorothiazide tablets therapy can be continued while heart failure is treated with other drugs.

Abrupt Cessation of Therapy

Exacerbations of angina pectoris and, in some instances, myocardial infarction or ventricular arrhythmia, have been observed in patients with coronary artery disease following abrupt cessation of therapy with beta-blockers. Such patients should, therefore, be cautioned against interruption or discontinuation of therapy without the physician’s advice. Even in patients without overt coronary artery disease, it may be advisable to taper therapy with bisoprolol fumarate and hydrochlorothiazide tablets over approximately 1 week with the patient under careful observation. If withdrawal symptoms occur, beta-blocking agent therapy should be reinstituted, at least temporarily.

Peripheral Vascular Disease

Beta-blockers can precipitate or aggravate symptoms of arterial insufficiency in patients with peripheral vascular disease. Caution should be exercised in such individuals.

Bronchospastic Disease

PATIENTS WITH BRONCHOSPASTIC PULMONARY DISEASE SHOULD, IN GENERAL, NOT RECEIVE BETA-BLOCKERS. Because of the relative beta1-selectivity of bisoprolol fumarate, bisoprolol fumarate and hydrochlorothiazide tablets may be used with caution in patients with bronchospastic disease who do not respond to, or who cannot tolerate other antihypertensive treatment. Since beta1-selectivity is not absolute, the lowest possible dose of bisoprolol fumarate and hydrochlorothiazide tablets should be used. A beta2 agonist (bronchodilator) should be made available.

Major Surgery

Chronically administered beta-blocking therapy should not be routinely withdrawn prior to major surgery; however, the impaired ability of the heart to respond to reflex adrenergic stimuli may augment the risks of general anesthesia and surgical procedures.

Hypoglycemia

Beta-blockers may prevent early warning signs of hypoglycemia, such as tachycardia, and increase the risk for severe or prolonged hypoglycemia at any time during treatment, especially in patients with diabetes mellitus or children and patients who are fasting (i.e., surgery, not eating regularly, or are vomiting). If severe hypoglycemia occurs, patients should be instructed to seek emergency treatment. Also, latent diabetes mellitus may become manifest and diabetic patients given thiazides may require adjustment of their insulin dose.

Thyrotoxicosis

Beta-adrenergic blockade may mask clinical signs of hyperthyroidism, such as tachycardia. Abrupt withdrawal of beta-blockade may be followed by an exacerbation of the symptoms of hyperthyroidism or may precipitate thyroid storm.

Renal Disease

Cumulative effects of the thiazides may develop in patients with impaired renal function. In such patients, thiazides may precipitate azotemia. In subjects with creatinine clearance less than 40 mL/min, the plasma half-life of bisoprolol fumarate is increased up to threefold, as compared to healthy subjects. If progressive renal impairment becomes apparent, bisoprolol fumarate and hydrochlorothiazide tablets should be discontinued (See Pharmacokinetics and Metabolism).

Hepatic Disease

Bisoprolol fumarate and hydrochlorothiazide tablets should be used with caution in patients with impaired hepatic function or progressive liver disease. Thiazides may alter fluid and electrolyte balance, which may precipitate hepatic coma. Also, elimination of bisoprolol fumarate is significantly slower in patients with cirrhosis than in healthy subjects (See Pharmacokinetics and Metabolism).

Acute Angle-Closure Glaucoma with or without Acute Myopia and Choroidal Effusions

Hydrochlorothiazide, a sulfonamide, can cause an idiosyncratic reaction, resulting in acute angle-closure glaucoma and elevated intraocular pressure with or without a noticeable acute myopic shift and/or choroidal effusions. Symptoms may include acute onset of decreased visual acuity or ocular pain and typically occur within hours to weeks of drug initiation. Untreated, the acute angle-closure glaucoma may result in permanent visual field loss. The primary treatment is to discontinue hydrochlorothiazide as rapidly as possible. Prompt medical or surgical treatments may need to be considered if the intraocular pressure remains uncontrolled. Risk factors for developing acute angle-closure glaucoma may include a history of sulfonamide or penicillin allergy.

PRECAUTIONS

General

Electrolyte and Fluid Balance Status

Although the probability of developing hypokalemia is reduced with bisoprolol fumarate and hydrochlorothiazide tablets because of the very low dose of HCTZ employed, periodic determination of serum electrolytes should be performed, and patients should be observed for signs of fluid or electrolyte disturbances, i.e., hyponatremia, hypochloremic alkalosis, hypokalemia, and hypomagnesemia. Thiazides have been shown to increase the urinary excretion of magnesium; this may result in hypomagnesemia.

Warning signs or symptoms of fluid and electrolyte imbalance include dryness of mouth, thirst, weakness, lethargy, drowsiness, restlessness, muscle pains or cramps, muscular fatigue, hypotension, oliguria, tachycardia, and gastrointestinal disturbances such as nausea and vomiting.

Hypokalemia may develop, especially with brisk diuresis when severe cirrhosis is present, during concomitant use of corticosteroids or adrenocorticotropic hormone (ACTH) or after prolonged therapy. Interference with adequate oral electrolyte intake will also contribute to hypokalemia. Hypokalemia and hypomagnesemia can provoke ventricular arrhythmias or sensitize or exaggerate the response of the heart to the toxic effects of digitalis. Hypokalemia may be avoided or treated by potassium supplementation or increased intake of potassium-rich foods.

Dilutional hyponatremia may occur in edematous patients in hot weather; appropriate therapy is water restriction rather than salt administration, except in rare instances when the hyponatremia is life threatening. In actual salt depletion, appropriate replacement is the therapy of choice.

Parathyroid Disease

Calcium excretion is decreased by thiazides, and pathologic changes in the parathyroid glands, with hypercalcemia and hypophosphatemia, have been observed in a few patients on prolonged thiazide therapy.

Hyperuricemia

Hyperuricemia or acute gout may be precipitated in certain patients receiving thiazide diuretics. Bisoprolol fumarate, alone or in combination with HCTZ, has been associated with increases in uric acid. However, in U.S. clinical trials, the incidence of treatment-related increases in uric acid was higher during therapy with HCTZ 25 mg (25%) than with B/H 6.25 mg (10%). Because of the very low dose of HCTZ employed, hyperuricemia may be less likely with bisoprolol fumarate and hydrochlorothiazide tablets.

Drug Interactions

Bisoprolol fumarate and hydrochlorothiazide tablets may potentiate the action of other antihypertensive agents used concomitantly. Bisoprolol fumarate and hydrochlorothiazide tablets should not be combined with other beta-blocking agents. Patients receiving catecholamine-depleting drugs, such as reserpine or guanethidine, should be closely monitored because the added beta-adrenergic blocking action of bisoprolol fumarate may produce excessive reduction of sympathetic activity. In patients receiving concurrent therapy with clonidine, if therapy is to be discontinued, it is suggested that bisoprolol fumarate and hydrochlorothiazide tablets be discontinued for several days before the withdrawal of clonidine.

Bisoprolol fumarate and hydrochlorothiazide tablets should be used with caution when myocardial depressants or inhibitors of AV conduction, such as certain calcium antagonists (particularly of the phenylalkylamine [verapamil] and benzothiazepine [diltiazem] classes), or antiarrhythmic agents, such as disopyramide, are used concurrently.

Both digitalis glycosides and beta-blockers slow atrioventricular conduction and decrease heart rate. Concomitant use can increase the risk of bradycardia.

Bisoprolol Fumarate

Concurrent use of rifampin increases the metabolic clearance of bisoprolol fumarate, shortening its elimination half-life. However, initial dose modification is generally not necessary.

Pharmacokinetic studies document no clinically relevant interactions with other agents given concomitantly, including thiazide diuretics and cimetidine. There was no effect of bisoprolol fumarate on prothrombin times in patients on stable doses of warfarin.

Risk of Anaphylactic Reaction

While taking beta-blockers, patients with a history of severe anaphylactic reaction to a variety of allergens may be more reactive to repeated challenge, either accidental, diagnostic, or therapeutic. Such patients may be unresponsive to the usual doses of epinephrine used to treat allergic reactions.

Hydrochlorothiazide

When given concurrently the following drugs may interact with thiazide diuretics.

Alcohol, barbiturates, or narcotics - potentiation of orthostatic hypotension may occur.

Antidiabetic drugs (oral agents and insulin) - dosage adjustment of the antidiabetic drug may be required.

Other antihypertensive drugs - additive effect or potentiation.

Cholestyramine and colestipol resins - Absorption of hydrochlorothiazide is impaired in the presence of anionic exchange resins. Single doses of cholestyramine and colestipol resins bind the hydrochlorothiazide and reduce its absorption in the gastrointestinal tract by up to 85 percent and 43 percent, respectively.

Corticosteroids, ACTH - Intensified electrolyte depletion, particularly hypokalemia.

Pressor amines (e.g., norepinephrine) - possible decreased response to pressor amines but not sufficient to preclude their use.

Skeletal muscle relaxants, nondepolarizing (e.g., tubocurarine) - possible increased responsiveness to the muscle relaxant.

Lithium - generally should not be given with diuretics. Diuretic agents reduce the renal clearance of lithium and add a high risk of lithium toxicity. Refer to the package insert for lithium preparations before use of such preparations with bisoprolol fumarate and hydrochlorothiazide tablets.

Nonsteroidal anti-inflammatory drugs - In some patients, the administration of a nonsteroidal anti-inflammatory agent can reduce the diuretic, natriuretic, and antihypertensive effects of loop, potassium sparing, and thiazide diuretics. Therefore, when bisoprolol fumarate and hydrochlorothiazide tablets and nonsteroidal anti-inflammatory agents are used concomitantly, the patient should be observed closely to determine if the desired effect of the diuretic is obtained.

In patients receiving thiazides, sensitivity reactions may occur with or without a history of allergy or bronchial asthma. Photosensitivity reactions and possible exacerbation or activation of systemic lupus erythematosus have been reported in patients receiving thiazides. The antihypertensive effects of thiazides may be enhanced in the post-sympathectomy patient.

Laboratory Test Interactions

Based on reports involving thiazides, bisoprolol fumarate and hydrochlorothiazide tablets may decrease serum levels of protein-bound iodine without signs of thyroid disturbance.

Because it includes a thiazide, bisoprolol fumarate and hydrochlorothiazide tablets should be discontinued before carrying out tests for parathyroid function (see PRECAUTIONS - Parathyroid Disease).

INFORMATION FOR PATIENTS

Warn patients, especially those with coronary artery disease, against discontinuing use of bisoprolol fumarate and hydrochlorothiazide tablets without a physician’s supervision. Patients should also be advised to consult a physician if any difficulty in breathing occurs, or if they develop other signs or symptoms of congestive heart failure or excessive bradycardia.

Inform patients or caregivers that there is a risk of hypoglycemia when bisoprolol fumarate and hydrochlorothiazide tablets is given to patients who are fasting or who are vomiting. Monitor for symptoms of hypoglycemia.

Patients should know how they react to this medicine before they operate automobiles and machinery or engage in other tasks requiring alertness.

Advise patients that photosensitivity reactions have been reported with thiazides.

Non-melanoma Skin Cancer

Instruct patients taking hydrochlorothiazide to protect skin from the sun and undergo regular skin cancer screening.

Acute Angle-Closure Glaucoma

Instruct patients taking hydrochlorothiazide to immediately consult their healthcare provider if visual field defects, decreased visual acuity, or ocular pain occur.

Carcinogenesis

Bisoprolol Fumarate and Hydrochlorothiazide Tablets

Long-term studies have not been conducted with the bisoprolol fumarate/hydrochlorothiazide combination.

Bisoprolol Fumarate

Long-term studies were conducted with oral bisoprolol fumarate administered in the feed of mice (20 and 24 months) and rats (26 months). No evidence of carcinogenic potential was seen in mice dosed up to 250 mg/kg/day or rats dosed up to 125 mg/kg/day. On a body weight basis, these doses are 625 and 312 times, respectively, the maximum recommended human dose (MRHD) of 20 mg, or 0.4 mg/kg/day, based on 50 kg individuals; on a body surface area basis, these doses are 59 times (mice) and 64 times (rats) the MRHD.

Hydrochlorothiazide

Two-year feeding studies in mice and rats, conducted under the auspices of the National Toxicology Program (NTP), treated mice and rats with doses of hydrochlorothiazide up to 600 and 100 mg/kg/day, respectively. On a body weight basis, these doses are 2400 times (in mice) and 400 times (in rats) the MRHD of hydrochlorothiazide (12.5 mg/day) in bisoprolol fumarate and hydrochlorothiazide tablets. On a body surface area basis, these doses are 226 times (in mice) and 82 times (in rats) the MRHD. These studies uncovered no evidence of carcinogenic potential of hydrochlorothiazide in rats or female mice, but there was equivocal evidence of hepatocarcinogenicity in male mice.

Mutagenesis

Bisoprolol Fumarate and Hydrochlorothiazide Tablets

The mutagenic potential of the bisoprolol fumarate/hydrochlorothiazide combination was evaluated in the microbial mutagenicity (Ames) test, the point mutation and chromosomal aberration assays in Chinese hamster V79 cells, and the micronucleus test in mice. There was no evidence of mutagenic potential in these in vitro and in vivo assays.

Bisoprolol Fumarate

The mutagenic potential of bisoprolol fumarate was evaluated in the microbial mutagenicity (Ames) test, the point mutation and chromosome aberration assays in Chinese hamster V79 cells, the unscheduled DNA synthesis test, the micronucleus test in mice, and the cytogenetics assay in rats. There was no evidence of mutagenic potential in these in vitro and in vivo assays.

Hydrochlorothiazide

Hydrochlorothiazide was not genotoxic in in vitro assays using strains TA 98, TA 100, TA 1535, TA 1537 and TA 1538 of Salmonella typhimurium (the Ames test); in the Chinese Hamster Ovary (CHO) test for chromosomal aberrations; or in in vivo assays using mouse germinal cell chromosomes, Chinese hamster bone marrow chromosomes, and the Drosophila sex-linked recessive lethal trait gene. Positive test results were obtained in the in vitro CHO Sister Chromatid Exchange (clastogenicity) test and in the mouse Lymphoma Cell (mutagenicity) assays, using concentrations of hydrochlorothiazide of 43-1300 µg/mL. Positive test results were also obtained in the Aspergillus nidulans non-disjunction assay, using an unspecified concentration of hydrochlorothiazide.

Impairment of Fertility

Bisoprolol Fumarate and Hydrochlorothiazide Tablets

Reproduction studies in rats did not show any impairment of fertility with the bisoprolol fumarate/hydrochlorothiazide combination doses containing up to 30 mg/kg/day of bisoprolol fumarate in combination with 75 mg/kg/day of hydrochlorothiazide. On a body weight basis, these doses are 75 and 300 times, respectively, the MRHD of bisoprolol fumarate and hydrochlorothiazide. On a body surface area basis, these study doses are 15 and 62 times, respectively, MRHD.

Bisoprolol Fumarate

Reproduction studies in rats did not show any impairment of fertility at doses up to 150 mg/kg/day of bisoprolol fumarate, or 375 and 77 times the MRHD on the basis of body weight and body surface area, respectively.

Hydrochlorothiazide

Hydrochlorothiazide had no adverse effects on the fertility of mice and rats of either sex in studies wherein these species were exposed, via their diet, to doses of up to 100 and 4 mg/kg/day, respectively, prior to mating and throughout gestation. Corresponding multiples of maximum recommended human doses are 400 (mice) and 16 (rats) on the basis of body weight and 38 (mice) and 3.3 (rats) on the basis of body surface area.

Teratogenic Effects

Bisoprolol Fumarate and Hydrochlorothiazide Tablets

In rats, the bisoprolol fumarate/hydrochlorothiazide (B/H) combination was not teratogenic at doses up to 51.4 mg/kg/day of bisoprolol fumarate in combination with 128.6 mg/kg/day of hydrochlorothiazide. Bisoprolol fumarate and hydrochlorothiazide doses used in the rat study are, as multiples of the MRHD in the combination, 129 and 514 times greater, respectively, on a body weight basis, and 26 and 106 times greater, respectively, on the basis of body surface area. The drug combination was maternotoxic (decreased body weight and food consumption) at B5.7/H14.3 (mg/kg/day) and higher, and fetotoxic (increased late resorptions) at B17.1/H42.9 (mg/kg/day) and higher. Maternotoxicity was present at 14/57 times the MRHD of B/H, respectively, on a body weight basis, and 3/12 times the MRHD of B/H doses, respectively, on the basis of body surface area. Fetotoxicity was present at 43/172 times the MRHD of B/H, respectively, on a body weight basis, and 9/35 times the MRHD of B/H doses, respectively, on the basis of body surface area. In rabbits, the B/H combination was not teratogenic at doses of B10/H25 (mg/kg/day). Bisoprolol fumarate and hydrochlorothiazide used in the rabbit study were not teratogenic at 25/100 times the B/H MRHD, respectively, on a body weight basis, and 10/40 times the B/H MRHD, respectively, on the basis of body surface area. The drug combination was maternotoxic (decreased body weight) at B1/H2.5 (mg/kg/day) and higher, and fetotoxic (increased resorptions) at B10/H25 (mg/kg/day). The multiples of the MRHD for the B/H combination that were maternotoxic are, respectively, 2.5/10 (on the basis of body weight) and 1/4 (on the basis of body surface area), and for fetotoxicity were, respectively 25/100 (on the basis of body weight) and 10/40 (on the basis of body surface area).

There are no adequate and well-controlled studies with bisoprolol fumarate and hydrochlorothiazide tablets in pregnant women. Bisoprolol fumarate and hydrochlorothiazide tablets should be used during pregnancy only if the potential benefit justifies the risk to the fetus.

Bisoprolol Fumarate

In rats, bisoprolol fumarate was not teratogenic at doses up to 150 mg/kg/day, which were 375 and 77 times the MRHD on the basis of body weight and body surface area, respectively. Bisoprolol fumarate was fetotoxic (increased late resorptions) at 50 mg/kg/day and maternotoxic (decreased food intake and body weight gain) at 150 mg/kg/day. The fetotoxicity in rats occurred at 125 times the MRHD on a body weight basis and 26 times the MRHD on the basis of body surface area. The maternotoxicity occurred at 375 times the MRHD on a body weight basis and 77 times the MRHD on the basis of body surface area. In rabbits, bisoprolol fumarate was not teratogenic at doses up to 12.5 mg/kg/day, which is 31 and 12 times the MRHD based on body weight and body surface area, respectively, but was embryolethal (increased early resorptions) at 12.5 mg/kg/day.

Hydrochlorothiazide

Hydrochlorothiazide was orally administered to pregnant mice and rats during respective periods of major organogenesis at doses up to 3000 and 1000 mg/kg/day, respectively. At these doses, which are multiples of the MRHD equal to 12,000 for mice and 4000 for rats, based on body weight, and equal to 1129 for mice and 824 for rats, based on body surface area, there was no evidence of harm to the fetus. There are, however, no adequate and well-controlled studies in pregnant women. Because animal reproduction studies are not always predictive of human response, this drug should be used during pregnancy only if clearly needed.

Nonteratogenic Effects

Thiazides cross the placental barrier and appear in the cord blood. The use of thiazides in pregnant women requires that the anticipated benefit be weighed against possible hazards to the fetus. These hazards include fetal or neonatal jaundice, pancreatitis, thrombocytopenia, and possibly other adverse reactions that have occurred in the adult.

Nursing Mothers

Bisoprolol fumarate alone or in combination with HCTZ has not been studied in nursing mothers. Thiazides are excreted in human breast milk. Small amounts of bisoprolol fumarate (<2% of the dose) have been detected in the milk of lactating rats. Because of the potential for serious adverse reactions in nursing infants, a decision should be made whether to discontinue nursing or to discontinue the drug, taking into account the importance of the drug to the mother.

Pediatric Use

Safety and effectiveness of bisoprolol fumarate and hydrochlorothiazide tablets in pediatric patients have not been established.

Geriatric Use

In clinical trials, at least 270 patients treated with bisoprolol fumarate plus HCTZ were 60 years of age or older. HCTZ added significantly to the antihypertensive effect of bisoprolol in elderly hypertensive patients. No overall differences in effectiveness or safety were observed between these patients and younger patients. Other reported clinical experience has not identified differences in responses between the elderly and younger patients, but greater sensitivity of some older individuals cannot be ruled out.

ADVERSE REACTIONS

Bisoprolol Fumarate and Hydrochlorothiazide Tablets

Bisoprolol fumarate/HCTZ 6.25 mg is well tolerated in most patients. Most adverse effects (AEs) have been mild and transient. In more than 65,000 patients treated worldwide with bisoprolol fumarate, occurrences of bronchospasm have been rare. Discontinuation rates for AEs were similar for bisoprolol fumarate/HCTZ 6.25 mg and placebo-treated patients.

In the United States, 252 patients received bisoprolol fumarate (2.5, 5, 10, or 40 mg)/HCTZ 6.25 mg and 144 patients received placebo in two controlled trials. In Study 1, bisoprolol fumarate 5/HCTZ 6.25 mg was administered for 4 weeks. In Study 2, bisoprolol fumarate 2.5, 10, or 40/HCTZ 6.25 mg was administered for 12 weeks. All adverse experiences, whether drug related or not, and drug related adverse experiences in patients treated with bisoprolol fumarate 2.5-10/HCTZ 6.25 mg, reported during comparable, 4-week treatment periods by at least 2% of bisoprolol fumarate/HCTZ 6.25 mg-treated patients (plus additional selected adverse experiences) are presented in the following table:

% of Patients with Adverse Experiencesa
Body System/ Adverse Experience | All Adverse Experiences |  | Drug Related Adverse Experiences
 | Placebob | B2.5-40/H6.25b | Placebob | B2.5-10/H6.25 b
 | (n=144) | (n=252) | (n=144) | (n=221)
 | % | % | % | %
Cardiovascular
bradycardia | 0.7 | 1.1 | 0.7 | 0.9
arrhythmia | 1.4 | 0.4 | 0.0 | 0.0
peripheral ischemia | 0.9 | 0.7 | 0.9 | 0.4
chest pain | 0.7 | 1.8 | 0.7 | 0.9
Respiratory
bronchospasm | 0.0 | 0.0 | 0.0 | 0.0
cough | 1.0 | 2.2 | 0.7 | 1.5
rhinitis | 2.0 | 0.7 | 0.7 | 0.9
URI | 2.3 | 2.1 | 0.0 | 0.0
Body as a Whole
asthenia | 0.0 | 0.0 | 0.0 | 0.0
fatigue | 2.7 | 4.6 | 1.7 | 3.0
peripheral edema | 0.7 | 1.1 | 0.7 | 0.9
Central Nervous System
dizziness | 1.8 | 5.1 | 1.8 | 3.2
headache | 4.7 | 4.5 | 2.7 | 0.4
Musculoskeletal
muscle cramps | 0.7 | 1.2 | 0.7 | 1.1
myalgia | 1.4 | 2.4 | 0.0 | 0.0
Psychiatric
insomnia | 2.4 | 1.1 | 2.0 | 1.2
somnolence | 0.7 | 1.1 | 0.7 | 0.9
loss of libido | 1.2 | 0.4 | 1.2 | 0.4
impotence | 0.7 | 1.1 | 0.7 | 1.1
Gastrointestinal
diarrhea | 1.4 | 4.3 | 1.2 | 1.1
nausea | 0.9 | 1.1 | 0.9 | 0.9
dyspepsia | 0.7 | 1.2 | 0.7 | 0.9

a Averages adjusted to combine across studies.

b Combined across studies.

Other adverse experiences that have been reported with the individual components are listed below.

Bisoprolol Fumarate

In clinical trials worldwide, or in postmarketing experience, a variety of other AEs, in addition to those listed above, have been reported. While in many cases it is not known whether a causal relationship exists between bisoprolol and these AEs, they are listed to alert the physician to a possible relationship.

Central Nervous System

Unsteadiness, dizziness, vertigo, headache, syncope, paresthesia, hypoesthesia, hyperesthesia, sleep disturbance/vivid dreams, insomnia, somnolence, depression, anxiety/restlessness, decreased concentration/memory.

Cardiovascular

Bradycardia, palpitations and other rhythm disturbances, cold extremities, claudication, hypotension, orthostatic hypotension, chest pain, congestive heart failure, dyspnea on exertion.

Gastrointestinal

Gastric/epigastric/abdominal pain, peptic ulcer, gastritis, dyspepsia, nausea, vomiting, diarrhea, constipation, dry mouth.

Musculoskeletal

Arthralgia, muscle/joint pain, back/neck pain, muscle cramps, twitching/tremor.

Skin

Rash, acne, eczema, psoriasis, skin irritation, pruritus, purpura, flushing, sweating, alopecia, dermatitis, exfoliative dermatitis (very rarely), cutaneous vasculitis.

Special Senses

Visual disturbances, ocular pain/pressure, abnormal lacrimation, tinnitus, decreased hearing, earache, taste abnormalities.

Metabolic

Gout.

Respiratory

Asthma, bronchospasm, bronchitis, dyspnea, pharyngitis, rhinitis, sinusitis, URI (upper respiratory infection).

Genitourinary

Decreased libido/impotence, Peyronie’s disease (very rarely), cystitis, renal colic, polyuria.

General

Fatigue, asthenia, chest pain, malaise, edema, weight gain, angioedema.

In addition, a variety of adverse effects have been reported with other beta-adrenergic blocking agents and should be considered potential adverse effects:

Central Nervous System

Reversible mental depression progressing to catatonia, hallucinations, an acute reversible syndrome characterized by disorientation to time and place, emotional lability, slightly clouded sensorium.

Allergic

Fever, combined with aching and sore throat, laryngospasm, and respiratory distress.

Hematologic

Agranulocytosis, thrombocytopenia.

Gastrointestinal

Mesenteric arterial thrombosis and ischemic colitis.

Miscellaneous

The oculomucocutaneous syndrome associated with the beta-blocker practolol has not been reported with bisoprolol fumarate during investigational use or extensive foreign marketing experience.

Hydrochlorothiazide

The following adverse experiences, in addition to those listed in the above table, have been reported with hydrochlorothiazide (generally with doses of 25 mg or greater).

General

Weakness.

Central Nervous System

Vertigo, paresthesia, restlessness.

Cardiovascular

Orthostatic hypotension (may be potentiated by alcohol, barbiturates, or narcotics).

Gastrointestinal

Anorexia, gastric irritation, cramping, constipation, jaundice (intrahepatic cholestatic jaundice), pancreatitis, cholecystitis, sialadenitis, dry mouth.

Musculoskeletal

Muscle spasm.

Hypersensitive Reactions

Purpura, photosensitivity, rash, urticaria, necrotizing angiitis (vasculitis and cutaneous vasculitis), fever, respiratory distress including pneumonitis and pulmonary edema, anaphylactic reactions.

Special Senses

Transient blurred vision, choroidal effusion, xanthopsia.

Metabolic

Gout.

Genitourinary

Sexual dysfunction, renal failure, renal dysfunction, interstitial nephritis.

Skin

Erythema multiforme including Stevens-Johnson syndrome, exfoliative dermatitis including toxic epidermal necrolysis.

Non-melanoma Skin Cancer

Hydrochlorothiazide is associated with an increased risk of non-melanoma skin cancer. In a study conducted in the Sentinel System, increased risk was predominantly for squamous cell carcinoma (SCC) and in white patients taking large cumulative doses. The increased risk for SCC in the overall population was approximately 1 additional case per 16,000 patients per year, and for white patients taking a cumulative dose of ≥50,000 mg the risk increase was approximately 1 additional SCC case for every 6,700 patients per year.

Bisoprolol Fumarate and Hydrochlorothiazide Tablets

Because of the low dose of hydrochlorothiazide in bisoprolol fumarate and hydrochlorothiazide tablets, adverse metabolic effects with bisoprolol fumarate/HCTZ 6.25 mg are less frequent and of smaller magnitude than with HCTZ 25 mg. Laboratory data on serum potassium from the U.S. placebo-controlled trials are shown in the following table:

Serum Potassium Data from U.S. Placebo Controlled Studies
 | Placeboa | B2.5/ H6.25 mg | B5/ H6.25 mg | B10/ H6.25 mg | HCTZ 25 mga
 | (N=130b) | (N=28b) | (N=149b) | (N=28b) | (N=142b)
Potassium
Mean Changec (mEq/L) | +0.04 | +0.11 | -0.08 | 0.00 | -0.30%
Hypokalemiad | 0.0% | 0.0% | 0.7% | 0.0% | 5.5%

a Combined across studies.

b Patients with normal serum potassium at baseline.

c Mean change from baseline at Week 4.

d Percentage of patients with abnormality at Week 4.

Treatment with both beta blockers and thiazide diuretics is associated with increases in uric acid. However, the magnitude of the change in patients treated with B/H 6.25 mg was smaller than in patients treated with HCTZ 25 mg. Mean increases in serum triglycerides were observed in patients treated with bisoprolol fumarate and hydrochlorothiazide 6.25 mg. Total cholesterol was generally unaffected, but small decreases in HDL cholesterol were noted.

Other laboratory abnormalities that have been reported with the individual components are listed below.

Bisoprolol Fumarate

In clinical trials, the most frequently reported laboratory change was an increase in serum triglycerides, but this was not a consistent finding.

Sporadic liver test abnormalities have been reported. In the U.S. controlled trials experience with bisoprolol fumarate treatment for 4-12 weeks, the incidence of concomitant elevations in SGOT and SGPT from 1 to 2 times normal was 3.9%, compared to 2.5% for placebo. No patient had concomitant elevations greater than twice normal.

In the long-term, uncontrolled experience with bisoprolol fumarate treatment for 6-18 months, the incidence of one or more concomitant elevations in SGOT and SGPT from 1 to 2 times normal was 6.2%. The incidence of multiple occurrences was 1.9%. For concomitant elevations in SGOT and SGPT of greater than twice normal, the incidence was 1.5%. The incidence of multiple occurrences was 0.3%. In many cases these elevations were attributed to underlying disorders, or resolved during continued treatment with bisoprolol fumarate.

Other laboratory changes included small increases in uric acid, creatinine, BUN, serum potassium, glucose, and phosphorus and decreases in WBC and platelets. There have been occasional reports of eosinophilia. These were generally not of clinical importance and rarely resulted in discontinuation of bisoprolol fumarate.

As with other beta-blockers, ANA conversions have also been reported on bisoprolol fumarate. About 15% of patients in long-term studies converted to a positive titer, although about one-third of these patients subsequently reconverted to a negative titer while on continued therapy.

Hydrochlorothiazide

Hyperglycemia, glycosuria, hyperuricemia, hypokalemia and other electrolyte imbalances (see PRECAUTIONS), hyperlipidemia, hypercalcemia, leukopenia, agranulocytosis, thrombocytopenia, aplastic anemia, and hemolytic anemia have been associated with HCTZ therapy.

OVERDOSAGE

There are limited data on overdose with bisoprolol fumarate and hydrochlorothiazide tablets. However, several cases of overdose with bisoprolol fumarate have been reported (maximum: 2000 mg). Bradycardia and/or hypotension were noted. Sympathomimetic agents were given in some cases, and all patients recovered.

The most frequently observed signs expected with overdosage of a beta-blocker are bradycardia and hypotension. Lethargy is also common, and with severe overdoses, delirium, coma, convulsions, and respiratory arrest have been reported to occur. Congestive heart failure, bronchospasm, and hypoglycemia may occur, particularly in patients with underlying conditions. With thiazide diuretics, acute intoxication is rare. The most prominent feature of overdose is acute loss of fluid and electrolytes. Signs and symptoms include cardiovascular (tachycardia, hypotension, shock), neuromuscular (weakness, confusion, dizziness, cramps of the calf muscles, paresthesia, fatigue, impairment of consciousness), gastrointestinal (nausea, vomiting, thirst), renal (polyuria, oliguria, or anuria [due to hemoconcentration]), and laboratory findings (hypokalemia, hyponatremia, hypochloremia, alkalosis, increased BUN [especially in patients with renal insufficiency]).

If overdosage of bisoprolol fumarate and hydrochlorothiazide tablets is suspected, therapy with bisoprolol fumarate and hydrochlorothiazide tablets should be discontinued and the patient observed closely. Treatment is symptomatic and supportive; there is no specific antidote. Limited data suggest bisoprolol fumarate is not dialyzable; similarly, there is no indication that hydrochlorothiazide is dialyzable. Suggested general measures include induction of emesis and/or gastric lavage, administration of activated charcoal, respiratory support, correction of fluid and electrolyte imbalance, and treatment of convulsions. Based on the expected pharmacologic actions and recommendations for other beta-blockers and hydrochlorothiazide, the following measures should be considered when clinically warranted:

Bradycardia

Administer IV atropine. If the response is inadequate, isoproterenol or another agent with positive chronotropic properties may be given cautiously. Under some circumstances, transvenous pacemaker insertion may be necessary.

Hypotension, Shock

The patient’s legs should be elevated. IV fluids should be administered and lost electrolytes (potassium, sodium) replaced. Intravenous glucagon may be useful. Vasopressors should be considered.

Heart Block (second or third degree)

Patients should be carefully monitored and treated with isoproterenol infusion or transvenous cardiac pacemaker insertion, as appropriate.

Congestive Heart Failure

Initiate conventional therapy (ie, digitalis, diuretics, vasodilating agents, inotropic agents).

Bronchospasm

Administer a bronchodilator such as isoproterenol and/or aminophylline.

Hypoglycemia

Administer IV glucose.

Surveillance

Fluid and electrolyte balance (especially serum potassium) and renal function should be monitored until normalized.

DOSAGE AND ADMINISTRATION

Bisoprolol is an effective treatment of hypertension in once-daily doses of 2.5 to 40 mg, while hydrochlorothiazide is effective in doses of 12.5 to 50 mg. In clinical trials of bisoprolol/hydrochlorothiazide combination therapy using bisoprolol doses of 2.5 to 20 mg and hydrochlorothiazide doses of 6.25 to 25 mg, the antihypertensive effects increased with increasing doses of either component.

The adverse effects (see WARNINGS) of bisoprolol are a mixture of dose-dependent phenomena (primarily bradycardia, diarrhea, asthenia, and fatigue) and dose-independent phenomena (eg, occasional rash); those of hydrochlorothiazide are a mixture of dose-dependent phenomena (primarily hypokalemia) and dose-independent phenomena (eg, possibly pancreatitis); the dose-dependent phenomena for each being much more common than the dose-independent phenomena. The latter consist of those few that are truly idiosyncratic in nature or those that occur with such low frequency that a dose relationship may be difficult to discern. Therapy with a combination of bisoprolol and hydrochlorothiazide will be associated with both sets of dose-independent adverse effects, and to minimize these, it may be appropriate to begin combination therapy only after a patient has failed to achieve the desired effect with monotherapy. On the other hand, regimens that combine low doses of bisoprolol and hydrochlorothiazide should produce minimal dose-dependent adverse effects, eg, bradycardia, diarrhea, asthenia and fatigue, and minimal dose-dependent adverse metabolic effects, ie, decreases in serum potassium (see CLINICAL PHARMACOLOGY).

Therapy Guided by Clinical Effect

A patient whose blood pressure is not adequately controlled with 2.5-20 mg bisoprolol daily may instead be given bisoprolol fumarate and hydrochlorothiazide tablets. Patients whose blood pressures are adequately controlled with 50 mg of hydrochlorothiazide daily, but who experience significant potassium loss with this regimen, may achieve similar blood pressure control without electrolyte disturbance if they are switched to bisoprolol fumarate and hydrochlorothiazide tablets.

Initial Therapy

Antihypertensive therapy may be initiated with the lowest dose of bisoprolol fumarate and hydrochlorothiazide tablets, one 2.5/6.25 mg tablet once daily. Subsequent titration (14-day intervals) may be carried out with bisoprolol fumarate and hydrochlorothiazide tablets up to the maximum recommended dose 20/12.5 mg (two 10/6.25 mg tablets) once daily, as appropriate.

Replacement Therapy

The combination may be substituted for the titrated individual components.

Cessation of Therapy

If withdrawal of bisoprolol fumarate and hydrochlorothiazide tablets therapy is planned, it should be achieved gradually over a period of about 2 weeks. Patients should be carefully observed.

Patients with Renal or Hepatic Impairment: As noted in the WARNINGS section, caution must be used in dosing/titrating patients with hepatic impairment or renal dysfunction. Since there is no indication that hydrochlorothiazide is dialyzable, and limited data suggest that bisoprolol is not dialyzable, drug replacement is not necessary in patients undergoing dialysis.

Geriatric Patients: Dosage adjustment on the basis of age is not usually necessary, unless there is also significant renal or hepatic dysfunction (see above and WARNINGS section).

Pediatric Patients: There is no pediatric experience with bisoprolol fumarate and hydrochlorothiazide tablets.

HOW SUPPLIED

Bisoprolol Fumarate and Hydrochlorothiazide - 2.5 mg/6.25 mg Tablets (bisoprolol fumarate 2.5 mg and hydrochlorothiazide 6.25 mg): Yellow, round, film-coated, unscored tablets. Debossed with stylized b within an engraved heart shape on one side and 47 on the other side, supplied as follows:

Bottle of 100 Tablets NDC 0093-3241-01

Bisoprolol Fumarate and Hydrochlorothiazide - 5 mg/6.25 mg Tablets (bisoprolol fumarate 5 mg and hydrochlorothiazide 6.25 mg): Pink, round, film-coated, unscored tablets. Debossed with stylized b within an engraved heart shape on one side and 50 on the other side, supplied as follows:

Bottle of 100 Tablets NDC 0093-3242-01

Bisoprolol Fumarate and Hydrochlorothiazide - 10 mg/6.25 mg Tablets (bisoprolol fumarate 10 mg and hydrochlorothiazide 6.25 mg): White, round, film-coated, unscored tablets. Debossed with stylized b within an engraved heart shape on one side and 40 on the other side, supplied as follows:

Bottle of 30 Tablets with child resistant closure NDC 0093-3243-56

Store at 20°C to 25°C (68°F to 77°F) [See USP Controlled Room Temperature].

Dispense in a tight container.

STORAGE AND HANDLING

Manufactured for:
Teva Pharmaceuticals
Parsippany, NJ 07054

BFHCTZ-004

Rev. 12/2023

Package/Label Display Panel

NDC 0093-3241-01

Bisoprolol Fumarate and Hydrochlorothiazide Tablets 2.5 mg/6.25 mg

Rx only 100 Tablets

Teva

Each tablet contains:

Bisoprolol fumarate 2.5 mg

Hydrochlorothiazide 6.25 mg

DOSAGE: For complete directions for use, see accompanying package brochure.

Package/Label Display Panel

NDC 0093-3242-01

Bisoprolol Fumarate and Hydrochlorothiazide Tablets 5 mg/6.25 mg

Rx only 100 Tablets

Teva

Each tablet contains:

Bisoprolol fumarate 5 mg

Hydrochlorothiazide 6.25 mg

DOSAGE: For complete directions for use, see accompanying package brochure.

Package/Label Display Panel

NDC 0093-3243-56

Bisoprolol Fumarate and Hydrochlorothiazide Tablets 10 mg/6.25 mg

Rx only 30 Tablets

Teva

Each tablet contains:

Bisoprolol fumarate 10 mg

Hydrochlorothiazide 6.25 mg

DOSAGE: For complete directions for use, see accompanying package brochure.